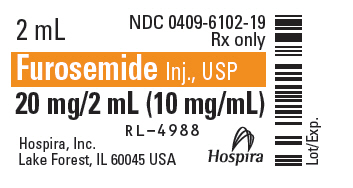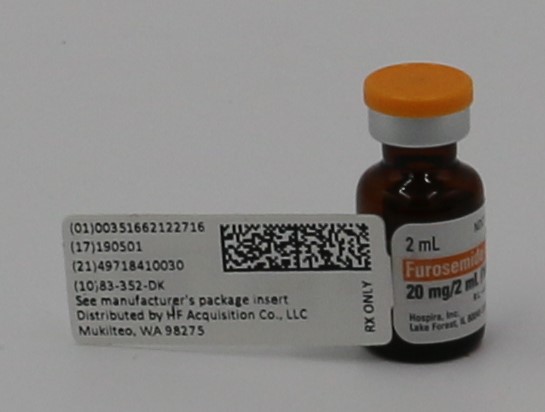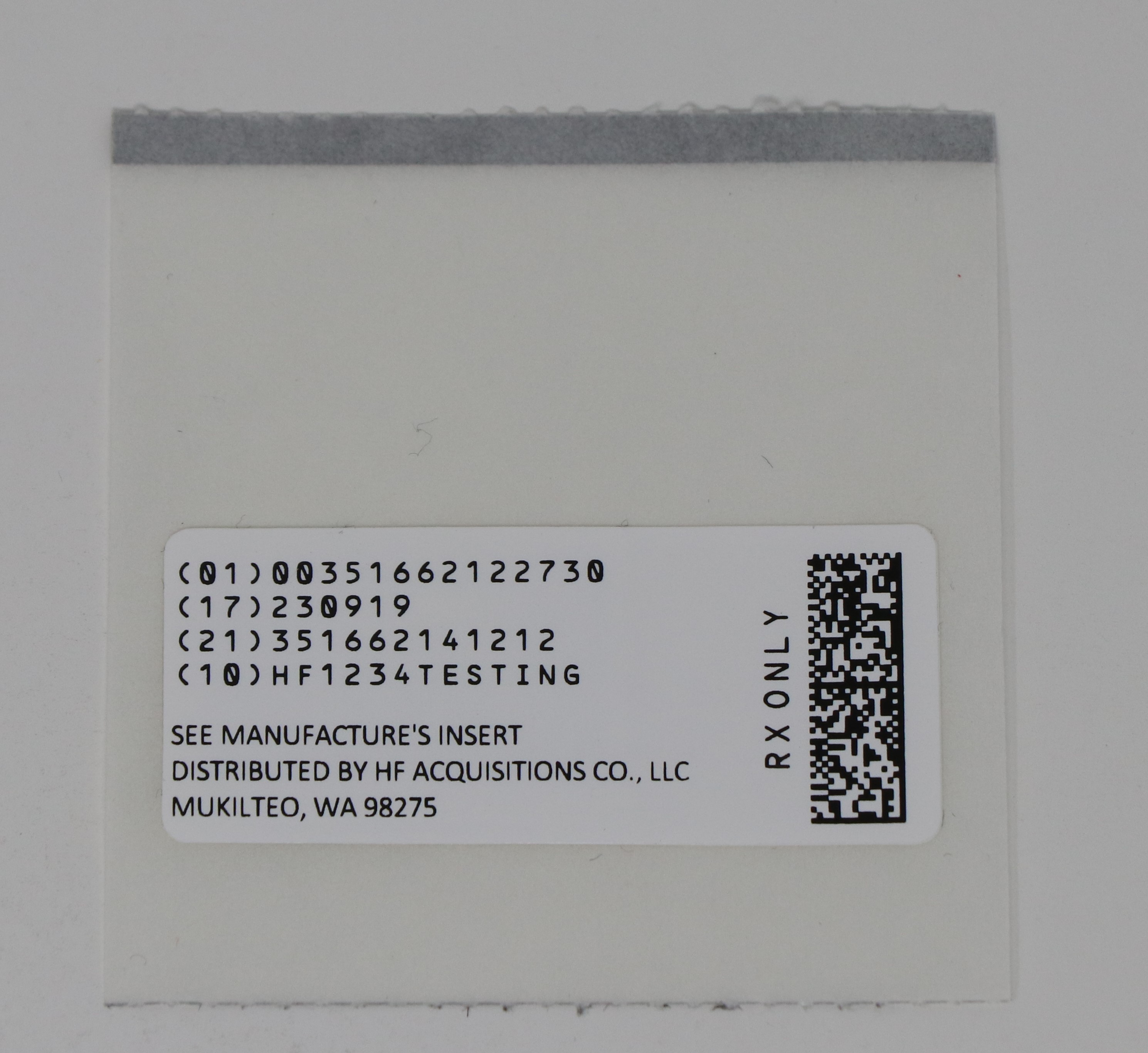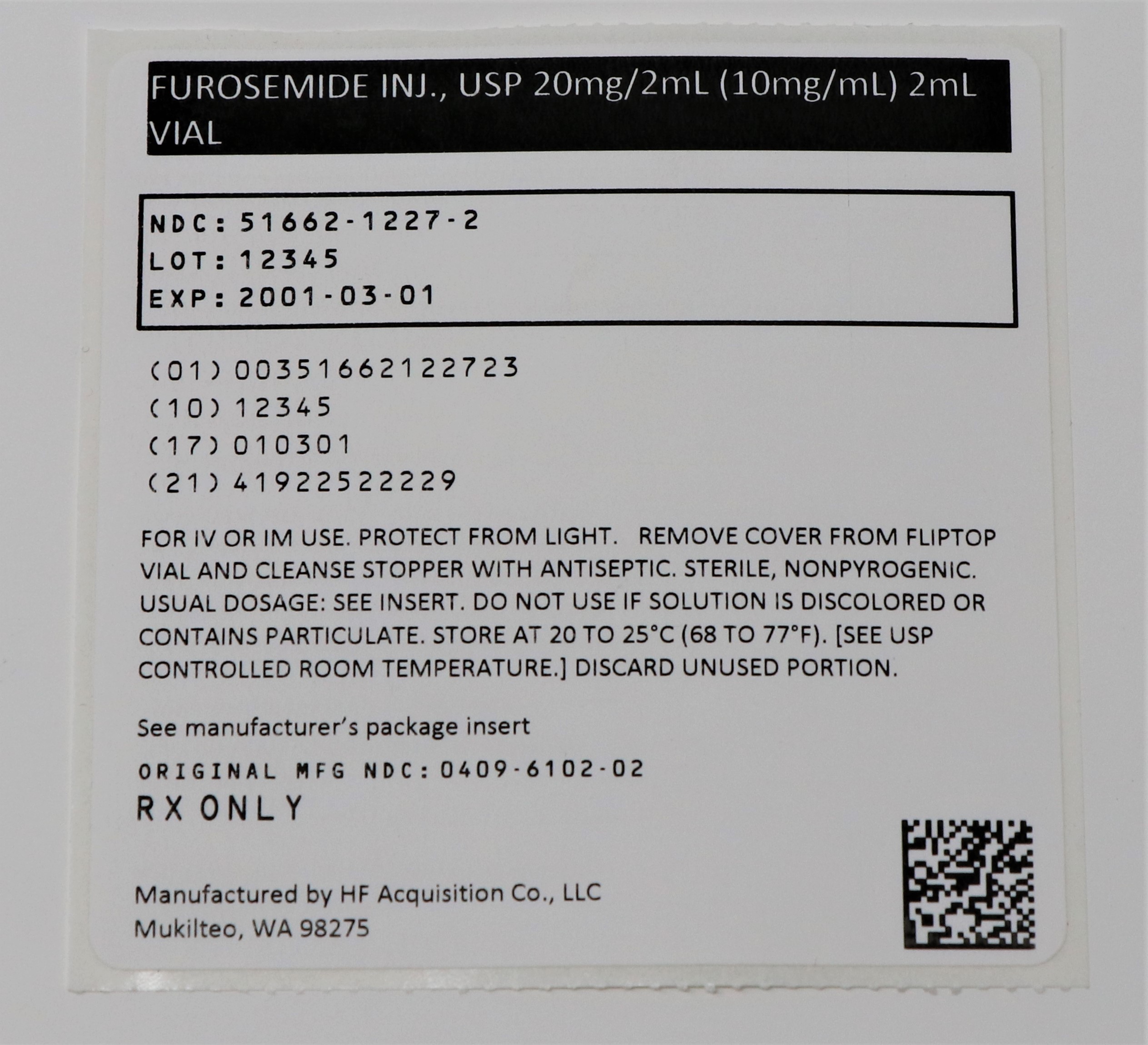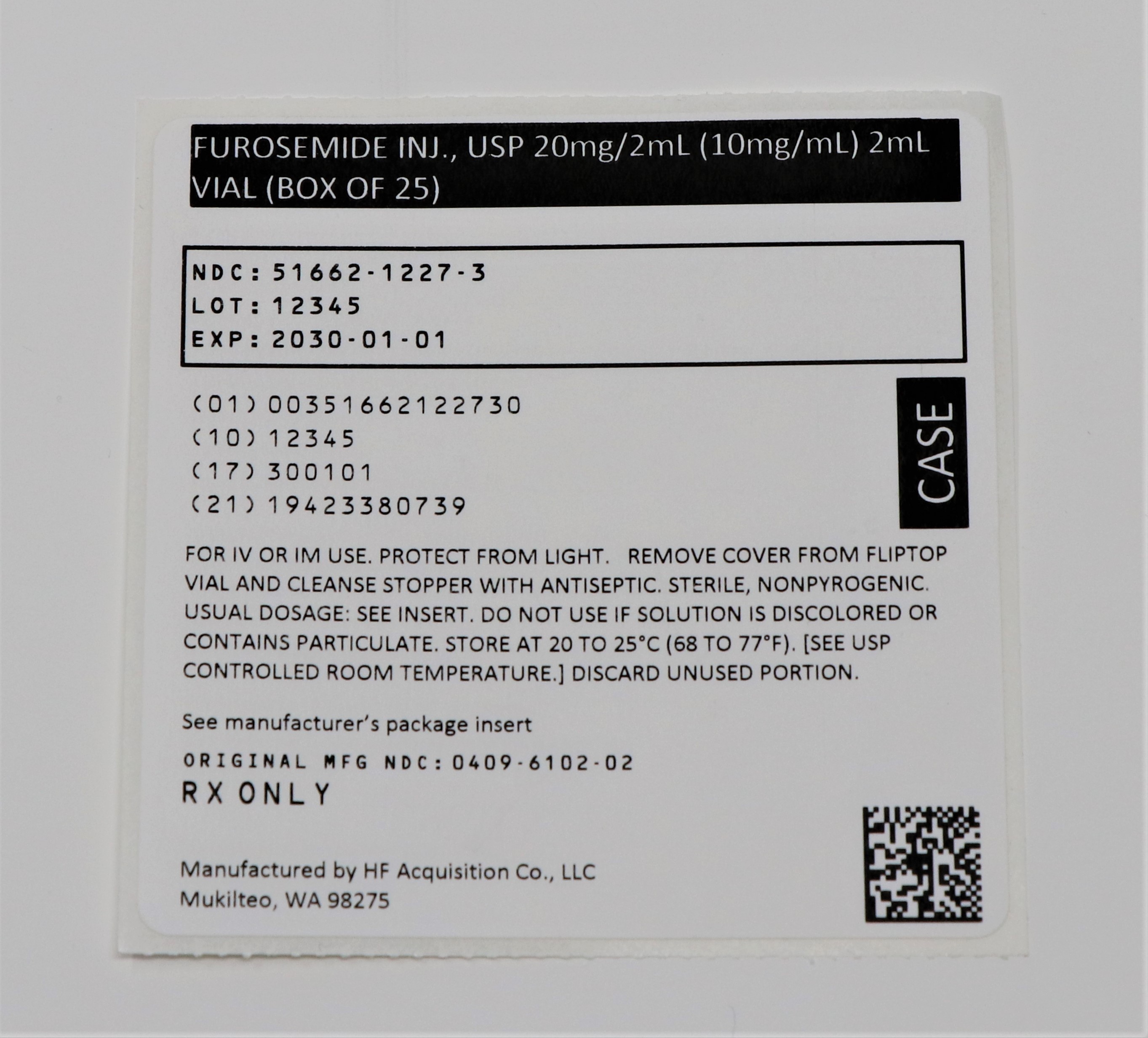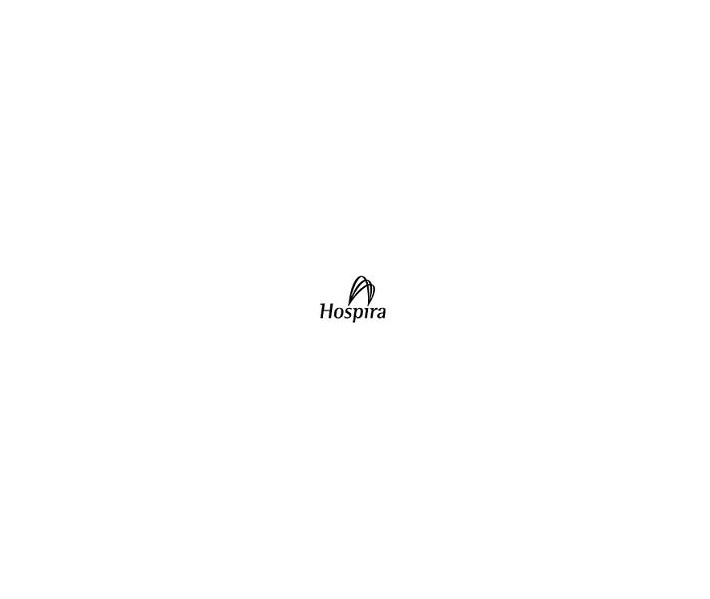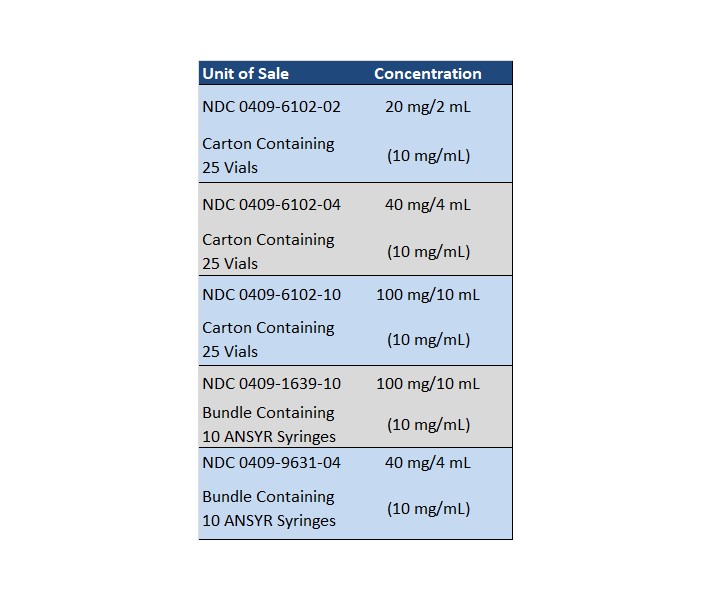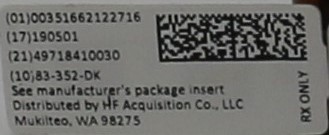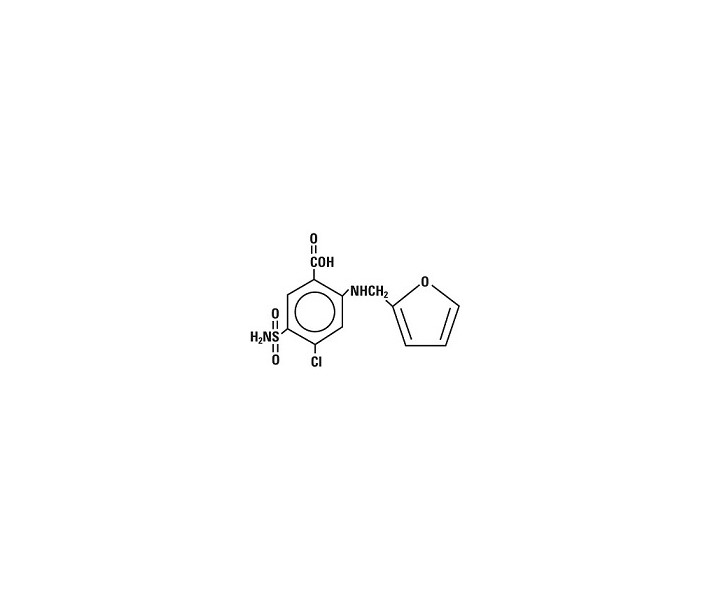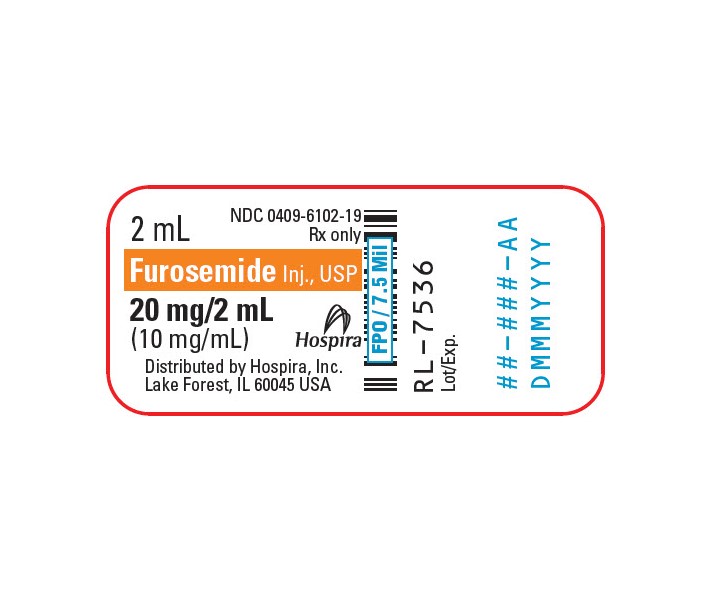 DRUG LABEL: FUROSEMIDE
NDC: 51662-1227 | Form: INJECTION, SOLUTION
Manufacturer: HF Acquisition Co LLC, DBA HealthFirst
Category: prescription | Type: HUMAN PRESCRIPTION DRUG LABEL
Date: 20240130

ACTIVE INGREDIENTS: FUROSEMIDE 10 mg/1 mL
INACTIVE INGREDIENTS: SODIUM CHLORIDE; WATER; SODIUM HYDROXIDE; HYDROCHLORIC ACID

FUROSEMIDE INJ., USP 20mg/2mL (10mg/mL) VIAL

SPL UNCLASSIFIED

Furosemide
Injection, USP

(10 mg/mL)

Fliptop Vial
Ansyr™ Plastic Syringe

Rx only

WARNING: Furosemide is a potent diuretic which, if given in excessive amounts, can lead to a profound diuresis with water and electrolyte depletion. Therefore, careful medical supervision is required and dose schedule must be adjusted to the individual patient's needs (see DOSAGE & ADMINISTRATION).

DESCRIPTION

Furosemide is a diuretic which is an anthranilic acid derivative. Chemically it is 4-chloro-N-furfuryl-5-sulfamoylanthranilic acid.

Furosemide is a white to slightly-yellow crystalline powder. It is practically insoluble in water, sparingly soluble in alcohol, freely soluble in dilute alkali solutions and insoluble in dilute acids. It has the following structural formula:

Molecular formula: C12H11CI N2O5S

Molecular weight: 330.75

Furosemide Injection, USP is a sterile solution intended for intramuscular or intravenous administration. Each mL contains furosemide 10 mg and sodium chloride sufficient to render solution isotonic in water for injection. Contains sodium hydroxide and may contain hydrochloric acid for pH adjustment. pH is 8.0 to 9.3.

The plastic syringe is molded from a specially formulated polypropylene. Water permeates from inside the container at an extremely slow rate which will have an insignificant effect on solution concentration over the expected shelf life.

Solutions in contact with the plastic container may leach out certain chemical components from the plastic in very small amounts; however, biological testing was supportive of the safety of the syringe material.

Contains no preservative.

CLINICAL PHARMACOLOGY

Investigations into the mode of action of furosemide have utilized micropuncture studies in rats, stop flow experiments in dogs and various clearance studies in both humans and experimental animals.

It has been demonstrated that furosemide inhibits primarily the reabsorption of sodium and chloride not only in the proximal and distal tubules but also in the loop of Henle. The high degree of efficacy is largely due to the unique site of action. The action on the distal tubule is independent of any inhibitory effect on carbonic anhydrase and aldosterone.

Recent evidence suggests that furosemide glucuronide is the only or at least the major biotransformation product of furosemide in man. Furosemide is extensively bound to plasma proteins, mainly to albumin. Plasma concentrations ranging from 1 to 400 mcg/mL are 91 to 99% bound in healthy individuals. The unbound fraction averages 2.3 to 4.1% at therapeutic concentrations.

The onset of diuresis following intravenous administration is within 5 minutes and somewhat later after intramuscular administration. The peak effect occurs within the first half hour. The duration of diuretic effect is approximately 2 hours.

In fasted normal men, the mean bioavailability of furosemide from tablets and oral solution is 64% and 60%, respectively, of that from an intravenous injection of the drug. Although furosemide is more rapidly absorbed from the oral solution (50 minutes) than from the tablet (87 minutes), peak plasma levels and area under the plasma concentration-time curves do not differ significantly. Peak plasma concentrations increase with increasing dose but times-to-peak do not differ among doses. The terminal half-life of furosemide is approximately 2 hours.

Significantly more furosemide is excreted in urine following the intravenous injection than after the tablet or oral solution. There are no significant differences between the two oral formulations in the amount of unchanged drug excreted in urine.

Geriatric Population

Furosemide binding to albumin may be reduced in elderly patients. Furosemide is predominantly excreted unchanged in the urine. The renal clearance of furosemide after intravenous administration in older healthy male subjects (60 to 70 years of age) is statistically significantly smaller than in younger healthy male subjects (20 to 35 years of age). The initial diuretic effect of furosemide in older subjects is decreased relative to younger subjects (see PRECAUTIONS, Geriatric Use).

INDICATIONS & USAGE

Parenteral therapy should be reserved for patients unable to take oral medication or for patients in emergency clinical situations.

Edema

Furosemide is indicated in adults and pediatric patients for the treatment of edema associated with congestive heart failure, cirrhosis of the liver and renal disease, including the nephrotic syndrome. Furosemide is particularly useful when an agent with greater diuretic potential is desired.

Furosemide is indicated as adjunctive therapy in acute pulmonary edema. The intravenous administration of furosemide is indicated when a rapid onset of diuresis is desired, e.g., in acute pulmonary edema.

If gastrointestinal absorption is impaired or oral medication is not practical for any reason, furosemide is indicated by the intravenous or intramuscular route. Parenteral use should be replaced with oral furosemide as soon as practical.

CONTRAINDICATIONS

Furosemide is contraindicated in patients with anuria and in patients with a history of hypersensitivity to furosemide.

WARNINGS

In patients with hepatic cirrhosis and ascites, furosemide therapy is best initiated in the hospital. In hepatic coma and in states of electrolyte depletion, therapy should not be instituted until the basic condition is improved. Sudden alterations of fluid and electrolyte balance in patients with cirrhosis may precipitate hepatic coma; therefore, strict observation is necessary during the period of diuresis. Supplemental potassium chloride and, if required, an aldosterone antagonist are helpful in preventing hypokalemia and metabolic alkalosis.

If increasing azotemia and oliguria occur during treatment of severe progressive renal disease, furosemide should be discontinued.

Cases of tinnitus and reversible or irreversible hearing impairment and deafness have been reported. Reports usually indicate that furosemide ototoxicity is associated with rapid injection, severe renal impairment, the use of higher than recommended doses, hypoproteinemia or concomitant therapy with aminoglycoside antibiotics, ethacrynic acid, or other ototoxic drugs. If the physician elects to use high dose parenteral therapy, controlled intravenous infusion is advisable (for adults, an infusion rate not exceeding 4 mg furosemide per minute has been used) (see PRECAUTIONS, Drug Interactions).

Pediatric Use

In premature neonates with respiratory distress syndrome, diuretic treatment with furosemide in the first few weeks of life may increase the risk of persistent patent ductus arteriosus (PDA), possibly through a prostaglandin-E-mediated process.

Literature reports indicate that premature infants with post conceptual age (gestational plus postnatal) less than 31 weeks receiving doses exceeding 1 mg/kg/24 hours may develop plasma levels which could be associated with potential toxic effects including ototoxicity.

Hearing loss in neonates has been associated with the use of furosemide injection (see WARNINGS, above).

PRECAUTIONS

General

Excessive diuresis may cause dehydration and blood volume reduction with circulatory collapse and possibly vascular thrombosis and embolism, particularly in elderly patients. As with any effective diuretic, electrolyte depletion may occur during furosemide therapy, especially in patients receiving higher doses and a restricted salt intake. Hypokalemia may develop with furosemide, especially with brisk diuresis, inadequate oral electrolyte intake, when cirrhosis is present, or during concomitant use of corticosteroids, ACTH, licorice in large amounts, or prolonged use of laxatives. Digitalis therapy may exaggerate metabolic effects of hypokalemia, especially myocardial effects.

All patients receiving furosemide therapy should be observed for these signs or symptoms of fluid or electrolyte imbalance (hyponatremia, hypochloremic alkalosis, hypokalemia, hypomagnesemia or hypocalcemia): dryness of mouth, thirst, weakness, lethargy, drowsiness, restlessness, muscle pains or cramps, muscular fatigue, hypotension, oliguria, tachycardia, arrhythmia, or gastrointestinal disturbances such as nausea and vomiting.

Increases in blood glucose and alterations in glucose tolerance tests (with abnormalities of the fasting and 2-hour postprandial sugar) have been observed, and rarely, precipitation of diabetes mellitus has been reported.

In patients with severe symptoms of urinary retention (because of bladder emptying disorders, prostatic hyperplasia, urethral narrowing), the administration of furosemide can cause acute urinary retention related to increased production and retention of urine. Thus, these patients require careful monitoring, especially during the initial stages of treatment.

In patients at high risk for radiocontrast nephropathy, furosemide can lead to a higher incidence of deterioration in renal function after receiving radiocontrast compared to high-risk patients who received only intravenous hydration prior to receiving radiocontrast.

In patients with hypoproteinemia (e.g., associated with nephrotic syndrome) the effect of furosemide may be weakened and its ototoxicity potentiated.

Asymptomatic hyperuricemia can occur and gout may rarely be precipitated.

Patients allergic to sulfonamides may also be allergic to furosemide.

The possibility exists of exacerbation or activation of systemic lupus erythematosus.

As with many other drugs, patients should be observed regularly for the possible occurrence of blood dyscrasias, liver or kidney damage, or other idiosyncratic reactions.

Information for Patients

Patients receiving furosemide should be advised that they may experience symptoms from excessive fluid and/or electrolyte losses. The postural hypotension that sometimes occurs can usually be managed by getting up slowly. Potassium supplements and/or dietary measures may be needed to control or avoid hypokalemia.

Patients with diabetes mellitus should be told that furosemide may increase blood glucose levels and thereby affect urine glucose tests. The skin of some patients may be more sensitive to the effects of sunlight while taking furosemide.

Hypertensive patients should avoid medications that may increase blood pressure, including over-the-counter products for appetite suppression and cold symptoms.

Laboratory Tests

Serum electrolytes (particularly potassium), CO2, creatinine and BUN should be determined frequently during the first few months of furosemide therapy and periodically thereafter.

Serum and urine electrolyte determinations are particularly important when the patient is vomiting profusely or receiving parenteral fluids. Abnormalities should be corrected or the drug temporarily withdrawn. Other medications may also influence serum electrolytes.

Reversible elevations of BUN may occur and are associated with dehydration, which should be avoided, particularly in patients with renal insufficiency.

Urine and blood glucose should be checked periodically in diabetics receiving furosemide, even in those suspected of latent diabetes.

Furosemide may lower serum levels of calcium (rarely cases of tetany have been reported) and magnesium. Accordingly, serum levels of these electrolytes should be determined periodically.

In premature infants furosemide may precipitate nephrocalcinosis/nephrolithiasis, therefore renal function must be monitored and renal ultrasonography performed (see PRECAUTIONS, Pediatric Use).

Drug Interactions

Furosemide may increase the ototoxic potential of aminoglycoside antibiotics, especially in the presence of impaired renal function. Except in life-threatening situations, avoid this combination.

Furosemide should not be used concomitantly with ethacrynic acid because of the possibility of ototoxicity. Patients receiving high doses of salicylates concomitantly with furosemide, as in rheumatic disease, may experience salicylate toxicity at lower doses because of competitive renal excretory sites.

There is a risk of ototoxic effects if cisplatin and furosemide are given concomitantly. In addition, nephrotoxicity of nephrotoxic drugs such as cisplatin may be enhanced if furosemide is not given in lower doses and with positive fluid balance when used to achieve forced diuresis during cisplatin treatment.

Furosemide has a tendency to antagonize the skeletal muscle relaxing effect of tubocurarine and may potentiate the action of succinylcholine.

Lithium generally should not be given with diuretics because they reduce lithium's renal clearance and add a high risk of lithium toxicity.

Furosemide combined with angiotensin converting enzyme inhibitors or angiotensin II receptor blockers may lead to severe hypotension and deterioration in renal function, including renal failure. An interruption or reduction in the dosage of furosemide, angiotensin converting enzyme inhibitors, or angiotensin receptor blockers may be necessary.

Potentiation occurs with ganglionic or peripheral adrenergic blocking drugs.

Furosemide may decrease arterial responsiveness to norepinephrine. However, norepinephrine may still be used effectively.

Simultaneous administration of sucralfate and Furosemide Injection may reduce the natriuretic and antihypertensive effects of furosemide. Patients receiving both drugs should be observed closely to determine if the desired diuretic and/or antihypertensive effect of furosemide is achieved. The intake of furosemide and sucralfate should be separated by at least 2 hours.

In isolated cases, intravenous administration of furosemide within 24 hours of taking chloral hydrate may lead to flushing, sweating attacks, restlessness, nausea, increase in blood pressure, and tachycardia. Use of furosemide concomitantly with chloral hydrate is therefore not recommended.

Phenytoin interferes directly with renal action of furosemide. There is evidence that treatment with phenytoin leads to decrease intestinal absorption of furosemide, and consequently to lower peak serum furosemide concentrations.

Methotrexate and other drugs that, like furosemide, undergo significant renal tubular secretion may reduce the effect of furosemide. Conversely, furosemide may decrease renal elimination of other drugs that undergo tubular secretion. High-dose treatment of both furosemide and these other drugs may result in elevated serum levels of these drugs and may potentiate their toxicity as well as the toxicity of furosemide.

Furosemide can increase the risk of cephalosporin-induced nephrotoxicity even in the setting of minor or transient renal impairment.

Concomitant use of cyclosporine and furosemide is associated with increased risk of gouty arthritis secondary to furosemide-induced hyperurecemia and cyclosporine impairment of renal urate excretion.

High doses (> 80 mg) of furosemide may inhibit the binding of thyroid hormones to carrier proteins and result in transient increase in free thyroid hormones, followed by an overall decrease in total thyroid hormone levels.

One study in six subjects demonstrated that the combination of furosemide and acetylsalicylic acid temporarily reduced creatinine clearance in patients with chronic renal insufficiency. There are case reports of patients who developed increased BUN, serum creatinine and serum potassium levels, and weight gain when furosemide was used in conjunction with NSAIDs.

Literature reports indicate that coadministration of indomethacin may reduce the natriuretic and antihypertensive effects of furosemide in some patients by inhibiting prostaglandin synthesis. Indomethacin may also affect plasma renin levels, aldosterone excretion, and renin profile evaluation. Patients receiving both indomethacin and furosemide should be observed closely to determine if the desired diuretic and/or antihypertensive effect of furosemide is achieved.

Carcinogenesis, Mutagenesis, Impairment of Fertility

Furosemide was tested for carcinogenicity by oral administration in one strain of mice and one strain of rats. A small but significantly increased incidence of mammary gland carcinomas occurred in female mice at a dose 17.5 times the maximum human dose of 600 mg. There were marginal increases in uncommon tumors in male rats at a dose of 15 mg/kg (slightly greater than the maximum human dose) but not at 30 mg/kg.

Furosemide was devoid of mutagenic activity in various strains of Salmonella typhimurium when tested in the presence or absence of an in vitro metabolic activation system, and questionably positive for gene mutation in mouse lymphoma cells in the presence of rat liver S9 at the highest dose tested. Furosemide did not induce sister chromatid exchange in human cells in vitro, but other studies on chromosomal aberrations in human cells in vitro gave conflicting results. In Chinese hamster cells it induced chromosomal damage but was questionably positive for sister chromatid exchange. Studies on the induction by furosemide of chromosomal aberrations in mice were inconclusive. The urine of rats treated with this drug did not induce gene conversion in Saccharomyces cerevisiae.

Furosemide produced no impairment of fertility in male or female rats, at 100 mg/kg/day (the maximum effective diuretic dose in the rat and 8 times the maximal human dose of 600 mg/day).

Pregnancy Teratogenic Effects

Furosemide has been shown to cause unexplained maternal deaths and abortions in rabbits at 2, 4, and 8 times the maximal recommended human oral dose. There are no adequate and well-controlled studies in pregnant women. Furosemide should be used during pregnancy only if the potential benefit justifies the potential risk to the fetus.

Treatment during pregnancy requires monitoring of fetal growth because of the potential for higher fetal birth weights.

The effects of furosemide on embryonic and fetal development and on pregnant dams were studied in mice, rats and rabbits.

Furosemide caused unexplained maternal deaths and abortions in the rabbit at the lowest dose of 25 mg/kg (2 times the maximal recommended human oral dose of 600 mg/day). In another study, a dose of 50 mg/kg (4 times the maximal recommended human oral dose of 600 mg/day) also caused maternal deaths and abortions when administered to rabbits between Days 12 and 17 of gestation. In a third study, none of the pregnant rabbits survived an oral dose of 100 mg/kg. Data from the above studies indicate fetal lethality that can precede maternal deaths.

The results of the mouse study and one of the three rabbit studies also showed an increased incidence and severity of hydronephrosis (distention of the renal pelvis and, in some cases, of the ureters) in fetuses derived from treated dams as compared with the incidence in fetuses from the control group.

Nursing Mothers

Because it appears in breast milk, caution should be exercised when furosemide is administered to a nursing mother.

Furosemide may inhibit lactation.

Pediatric Use

Renal calcifications (from barely visible on x-ray to staghorn) have occurred in some severely premature infants treated with intravenous furosemide for edema due to patent ductus arteriosus and hyaline membrane disease. The concurrent use of chlorothiazide has been reported to decrease hypercalcinuria and dissolve some calculi.

In premature infants furosemide may precipitate nephrocalcinosis/nephrolithiasis. Nephrocalcinosis/nephrolithiasis has also been observed in children under 4 years of age with no history of prematurity who have been treated chronically with furosemide. Monitor renal function, and renal ultrasonography should be considered, in pediatric patients receiving furosemide.

If furosemide is administered to premature infants during the first weeks of life, it may increase the risk of persistence of patent ductus arteriosus.

Geriatric Use

Controlled clinical studies of furosemide did not include sufficient numbers of subjects aged 65 and over to determine whether they respond differently from younger subjects. Other reported clinical experience has not identified differences in responses between the elderly and younger patients. In general, dose selection for the elderly patient should be cautious, usually starting at the low end of the dosing range, reflecting the greater frequency of decreased hepatic, renal or cardiac function, and of concomitant disease or other drug therapy.

This drug is known to be substantially excreted by the kidney, and the risk of toxic reactions to this drug may be greater in patients with impaired renal function. Because elderly patients are more likely to have decreased renal function, care should be taken in dose selection and it may be useful to monitor renal function (see PRECAUTIONS, General and DOSAGE & ADMINISTRATION).

ADVERSE REACTIONS

Adverse reactions are categorized below by organ system and listed by decreasing severity.

Gastrointestinal System Reactions

(1) Hepatic encephalopathy in patients with hepatocellular insufficiency (2) Pancreatitis (3) Jaundice (intrahepatic cholestatic jaundice) (4) Increased liver enzymes (5) Anorexia (6) Oral and gastric irritation (7) Cramping (8) Diarrhea (9) Constipation (10) Nausea (11) Vomiting

Systemic Hypersensitivity Reactions

(1) Severe anaphylactic or anaphylactoid reactions (e.g., with shock) (2) Systemic vasculitis (3) Interstitial nephritis (4) Necrotizing angiitis

Central Nervous System Reactions

(1) Tinnitus and hearing loss (2) Paresthesias (3) Vertigo (4) Dizziness (5) Headache (6) Blurred vision (7) Xanthopsia

Hematologic Reactions

(1) Aplastic anemia (2)Thrombocytopenia (3) Agranulocytosis (4) Hemolytic anemia (5) Leukopenia (6) Anemia (7) Eosinophilia.

Dermatologic-Hypersensitivity Reactions

(1) Toxic epidermal necrolysis (2) Stevens-Johnson Syndrome (3) Erythema multiforme (4) Drug rash with eosinophila and systemic symptoms (5) Acute generalized exanthematous pustulosis (6) Exfoliative dermatitis (7) Bullous pemphigoid (8) Purpura (9) Photosensitivity (10) Rash (11) Pruritus (12) Urticaria

Cardiovascular Reactions

(1) Orthostatic hypotension may occur and be aggravated by alcohol, barbiturates or narcotics (2) Increase in cholesterol and triglyceride serum levels

Other Reactions

(1) Hyperglycemia (2) Glycosuria (3) Hyperuricemia (4) Muscle spasm (5) Weakness (6) Restlessness (7) Urinary bladder spasm (8) Thrombophlebitis (9) Transient injection site pain following intramuscular injection (10) Fever.

Whenever adverse reactions are moderate or severe, furosemide dosage should be reduced or therapy withdrawn.

OVERDOSAGE

The principal signs and symptoms of overdose with furosemide are dehydration, blood volume reduction, hypotension, electrolyte imbalance, hypokalemia and hypochloremic alkalosis, and are extensions of its diuretic action.

The acute toxicity of furosemide has been determined in mice, rats and dogs. In all three, the oral LD50 exceeded 1,000 mg/kg body weight, while the intravenous LD50 ranged from 300 to 680 mg/kg. The acute intragastric toxicity in neonatal rats is 7 to 10 times that of adult rats.

The concentration of furosemide in biological fluids associated with toxicity or death is not known.

Treatment of overdosage is supportive and consists of replacement of excessive fluid and electrolyte losses. Serum electrolytes, carbon dioxide level and blood pressure should be determined frequently. Adequate drainage must be assured in patients with urinary bladder outlet obstruction (such as prostatic hypertrophy).

Hemodialysis does not accelerate furosemide elimination.

DOSAGE & ADMINISTRATION

Adults

Parenteral therapy with Furosemide Injection, USP should be used only in patients unable to take oral medication or in emergency situations and should be replaced with oral therapy as soon as practical.

Edema

The usual initial dose of furosemide is 20 to 40 mg given as a single dose, injected intramuscularly or intravenously. The intravenous dose should be given slowly (1 to 2 minutes). Ordinarily a prompt diuresis ensues. If needed, another dose may be administered in the same manner 2 hours later or the dose may be increased. The dose may be raised by 20 mg and given not sooner than 2 hours after the previous dose until the desired diuretic effect has been obtained. This individually determined single dose should then be given once or twice daily.

Therapy should be individualized according to patient response to gain maximal therapeutic response and to determine the minimal dose needed to maintain that response. Close medical supervision is necessary.

When furosemide is given for prolonged periods, careful clinical observation and laboratory monitoring are particularly advisable (see PRECAUTIONS: Laboratory Tests).

If the physician elects to use high dose parenteral therapy, add the furosemide to either Sodium Chloride Injection, USP, Lactated Ringer's Injection, USP, or Dextrose Injection 5%, USP, after pH has been adjusted to above 5.5, and administer as a controlled intravenous infusion at a rate not greater than 4 mg/min. Furosemide Injection is a buffered alkaline solution with a pH of about 9 and the drug may precipitate at pH values below 7. Care must be taken to ensure that the pH of the prepared infusion solution is in the weakly alkaline to neutral range. Acid solutions, including other parenteral medications (e.g., labetalol, ciprofloxacin, amrinone, milrinone) must not be administered concurrently in the same infusion because they may cause precipitation of the furosemide. In addition, furosemide injection should not be added to a running intravenous line containing any of these acidic products.

Acute Pulmonary Edema

The usual initial dose of furosemide is 40 mg injected slowly intravenously (over 1 to 2 minutes). If a satisfactory response does not occur within 1 hour, the dose may be increased to 80 mg injected slowly intravenously (over 1 to 2 minutes).

If necessary, additional therapy (e.g., digitalis, oxygen) may be administered concomitantly.

Geriatric patients

In general, dose selection for the elderly patient should be cautious, usually starting at the low end of the dosing range (see PRECAUTIONS, Geriatric Use).

Pediatric Patients

Parenteral therapy should be used only in patients unable to take oral medication or in emergency situations and should be replaced with oral therapy as soon as practical.

The usual initial dose of furosemide injection (intravenously or intramuscularly) in pediatric patients is 1 mg/kg body weight and should be given slowly under close medical supervision. If the diuretic response to the initial dose is not satisfactory, dosage may be increased by 1 mg/kg not sooner than 2 hours after the previous dose, until the desired diuretic effect has been obtained. Doses greater than 6 mg/kg body weight are not recommended.

Literature reports suggest that the maximum dose for premature infants should not exceed 1 mg/kg/day (see WARNINGS, Pediatric Use).

Furosemide Injection should be inspected visually for particulate matter and discoloration before administration. Do not use if solution is discolored.

To prevent needle-stick injuries, needles should not be recapped, purposely bent, or broken by hand.

HOW SUPPLIED

FUROSEMIDE INJ., USP is supplied in the following dosage forms.
NDC 51662-1227-1
FUROSEMIDE INJ., USP 20mg/2mL (10mg/mL) VIAL

NDC 51662-1227-2

Pouch containing a single FUROSEMIDE INJ., USP 20mg/2mL (10mg/mL) VIAL

NDC 51662-1227-3

Case of 25 pouches - FUROSEMIDE INJ., USP 20mg/2mL (10mg/mL) VIAL

HF Acquisition Co LLC, DBA HealthFirst
Mukilteo, WA 98275

Also supplied in the following manufacture supplied dosage forms

Furosemide Injection, USP 10 mg/mL is supplied as follows:

Store at 20 to 25°C (68 to 77°F). [See USP Controlled Room Temperature.]

Do not use if solution is discolored or contains particulate.

Protect from light. Do not remove the Ansyr syringe from carton until ready to use.

Discard unused portion.

Distributed by Hospira, Inc., Lake Forest, IL 60045 USA

LAB-1025-3.0

05/2018

PRINCIPAL DISPLAY PANEL, VIAL

2 mL
NDC 0409-6102-19
Rx only

Furosemide Inj., USP

20 mg/2 mL (10 mg/mL)

RL-4988

Hospira, Inc.
Lake Forest, IL 60045 USA

Hospira